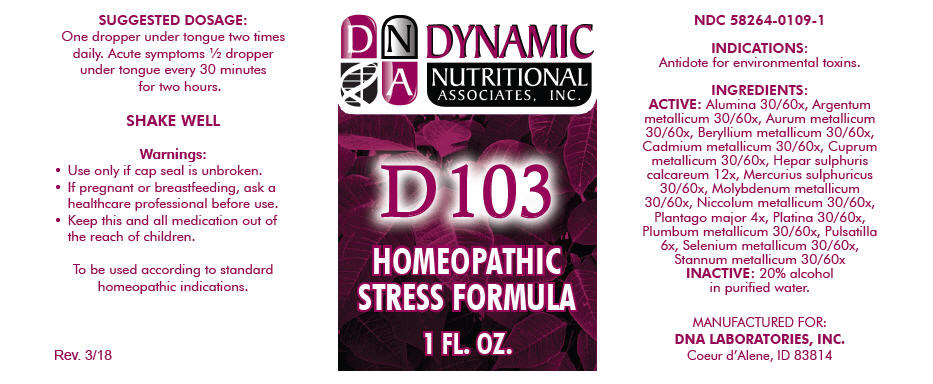 DRUG LABEL: D-103
NDC: 58264-0109 | Form: SOLUTION
Manufacturer: DNA Labs, Inc.
Category: homeopathic | Type: HUMAN OTC DRUG LABEL
Date: 20250113

ACTIVE INGREDIENTS: ALUMINUM OXIDE 30 [hp_X]/1 mL; SILVER 30 [hp_X]/1 mL; GOLD 30 [hp_X]/1 mL; BERYLLIUM 30 [hp_X]/1 mL; CADMIUM 30 [hp_X]/1 mL; COPPER 30 [hp_X]/1 mL; CALCIUM SULFIDE 12 [hp_X]/1 mL; MERCURIC SULFATE 30 [hp_X]/1 mL; MOLYBDENUM 30 [hp_X]/1 mL; NICKEL 30 [hp_X]/1 mL; PLANTAGO MAJOR 4 [hp_X]/1 mL; PLATINUM 30 [hp_X]/1 mL; LEAD 30 [hp_X]/1 mL; ANEMONE PRATENSIS 6 [hp_X]/1 mL; SELENIUM 30 [hp_X]/1 mL; TIN 30 [hp_X]/1 mL
INACTIVE INGREDIENTS: ALCOHOL; WATER

D-103

NDC 58264-0109-1

INDICATIONS

PURPOSE

Antidote for environmental toxins.

INGREDIENTS

ACTIVE

Alumina 30/60x, Argentum metallicum 30/60x, Aurum metallicum 30/60x, Beryllium metallicum 30/60x, Cadmium metallicum 30/60x, Cuprum metallicum 30/60x, Hepar sulphuris calcareum 12x, Mercurius sulphuricus 30/60x, Molybdenum metallicum 30/60x, Niccolum metallicum 30/60x, Plantago major 4x, Platina 30/60x, Plumbum metallicum 30/60x, Pulsatilla 6x, Selenium metallicum 30/60x, Stannum metallicum 30/60x

INACTIVE

20% alcohol in purified water.

SUGGESTED DOSAGE

One dropper under tongue two times daily. Acute symptoms ½ dropper under tongue every 30 minutes for two hours.

STORAGE AND HANDLING

SHAKE WELL

Warnings

- Use only if cap seal is unbroken.

PREGNANCY OR BREAST FEEDING

- If pregnant or breastfeeding, ask a healthcare professional before use.

KEEP OUT OF REACH OF CHILDREN

- Keep this and all medication out of the reach of children.

To be used according to standard homeopathic indications.

PRINCIPAL DISPLAY PANEL - 1 FL. OZ. Bottle Label

DYNAMIC
NUTRITIONAL
ASSOCIATES, INC.

D 103

HOMEOPATHIC
STRESS FORMULA

1 FL. OZ.